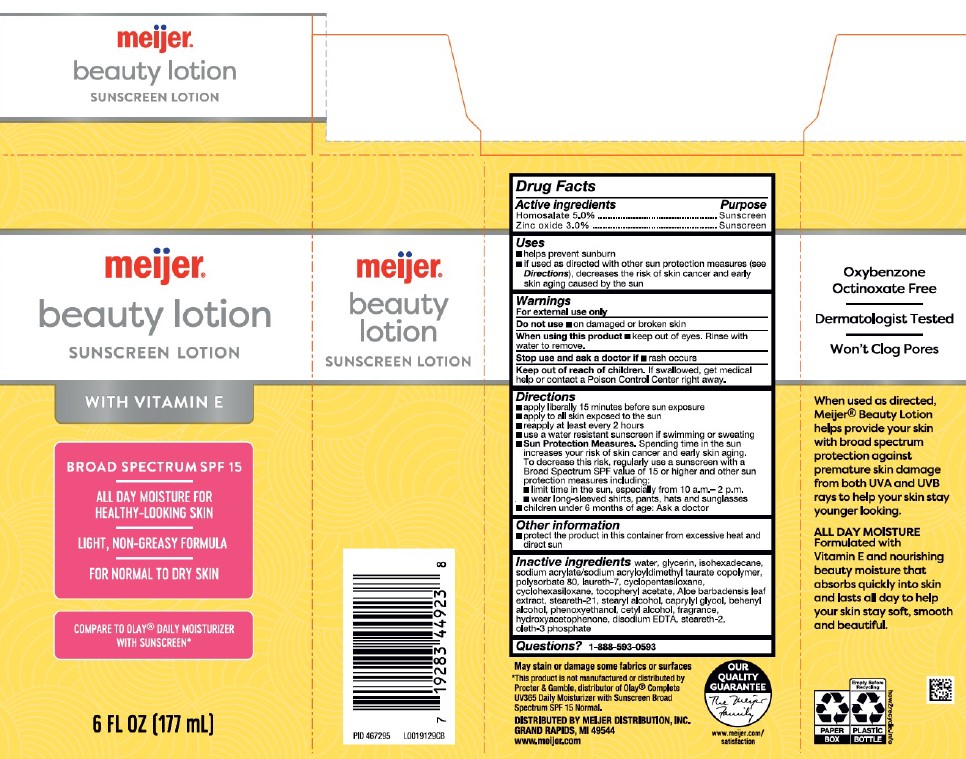 DRUG LABEL: Beauty Hydrating
NDC: 79481-0000 | Form: LOTION
Manufacturer: Meijer, Inc.
Category: otc | Type: HUMAN OTC DRUG LABEL
Date: 20260219

ACTIVE INGREDIENTS: HOMOSALATE 50 mg/1 mL; ZINC OXIDE 30 mg/1 mL
INACTIVE INGREDIENTS: WATER; GLYCERIN; ISOHEXADECANE; SODIUM ACRYLATE/SODIUM ACRYLOYLDIMETHYLTAURATE COPOLYMER (4000000 MW); POLYSORBATE 80; LAURETH-7; CYCLOMETHICONE 5; CYCLOMETHICONE 6; .ALPHA.-TOCOPHEROL ACETATE; ALOE VERA LEAF; STEARETH-21; STEARYL ALCOHOL; CAPRYLYL GLYCOL; DOCOSANOL; PHENOXYETHANOL; CETYL ALCOHOL; HYDROXYACETOPHENONE; EDETATE DISODIUM; STEARETH-2; OLETH-3 PHOSPHATE

Meijer 043.000/043AA
Original Beauty Lotion SPF 15

Active ingredients

Homosalate 5.0%

Zinc oxide 3.0%

Purpose

Sunscreen

Uses

- helps prevent sunburn
- if used as directed with other sun protection measures (see Directions), decreases the risk of skin cancer and early skin aging caused by the sun

Warnings

For external use only

Do not use

on damaged or broken skin

When using this product

- keep out of eyes. Rinse with water to remove.

Stop use and ask a doctor if

rash occurs

Keep out of reach of children.

If swallowed, get medical help or contact a Poison Control Center right away.

Directions

- apply liberally 15 minutes before sun exposure
- apply to all skin exposed to the sun
- reapply at least every 2 hours
- use a water resistant sunscreen if swimming or sweating
- Sun Protection Measures. Spending time in the sun increases your risk of skin cancer and early skin aging. To decrease this risk, regularly use a sunscreen with a Broad Spectrum SPF value of 15 or higher and other sun protection measures including:
- limit time in the sun, especially from 10 a.m.–2 p.m.
- wear long-sleeved shirts, pants, hats and sunglasses
- children under 6 months of age: Ask a doctor

Other information

- protect the product in this container from excessive heat and direct sun

Inactive ingredients

water, glycerin, isohexadecane, sodium acrylate/sodium acryloyldimethyl taurate copolymer, polysorbate 80, laureth-7, cyclopentasiloxane, cyclohexasiloxane, tocopheryl acetate, Aloe barbadensis leaf extract, steareth-21, stearyl alcohol, caprylyl glycol, behenyl alcohol, phenoxyethanol, cetyl alcohol, fragrance, hydroxyacetophenone, disodium EDTA, steareth-2, oleth-3 phosphate

Questions?

1-888-593-0593

Side panel claims

Oxybenzone & Octinoxate Free

Dermatologist Tested

Won't Clog Pores

When used as directed, Meijer® Beauty Lotion helps provide your skin with broad spectrum protection against premature skin damage from both UVA and UVB rays to help your skin stay younger looking.

ALL DAY MOISTURE

Formulated with Vitamin E and nourishing beauty moisture that absorbs quickly into skin and lasts all day to help your skin stay soft, smooth and beautiful.

Disclaimer

May stain or damage some fabric or surfaces

*This product is not manufactured or distributed by Procter & Gamble, distributor of Olay® Complete UV365 All Day Moisturizer with Sunscreen Broad Spectrum SPF 15 Normal.

Adverse reaction

DISTIBUTED BY MEIJER DISTRIBUTION, INC.

GRAND RAPIDS, MI 49544

www.meijer.com

OUR QUALITY GUARANTEE

The Meijer Family

www.meijer.com/satisfaction

PAPER BOX

Empty Before Recycling

PLASTIC BOTTLE

how2recycle.info

Principal display panel

meijer®

beauty lotion

SUNSCREEN LOTION

WITH VITAMIN E

BROAD SPECTRUM SPF 15

ALLL DAY MOISTURE FOR HEALTHY-LOOKING SKIN

LIGHT, NON-GREASY FORMULA

FOR NORMAL TO DRY SKIN

COMPARE TO OLAY® DAILY MOISTURIZER WITH SUNSCREEN*

6 FL OZ (177 mL)